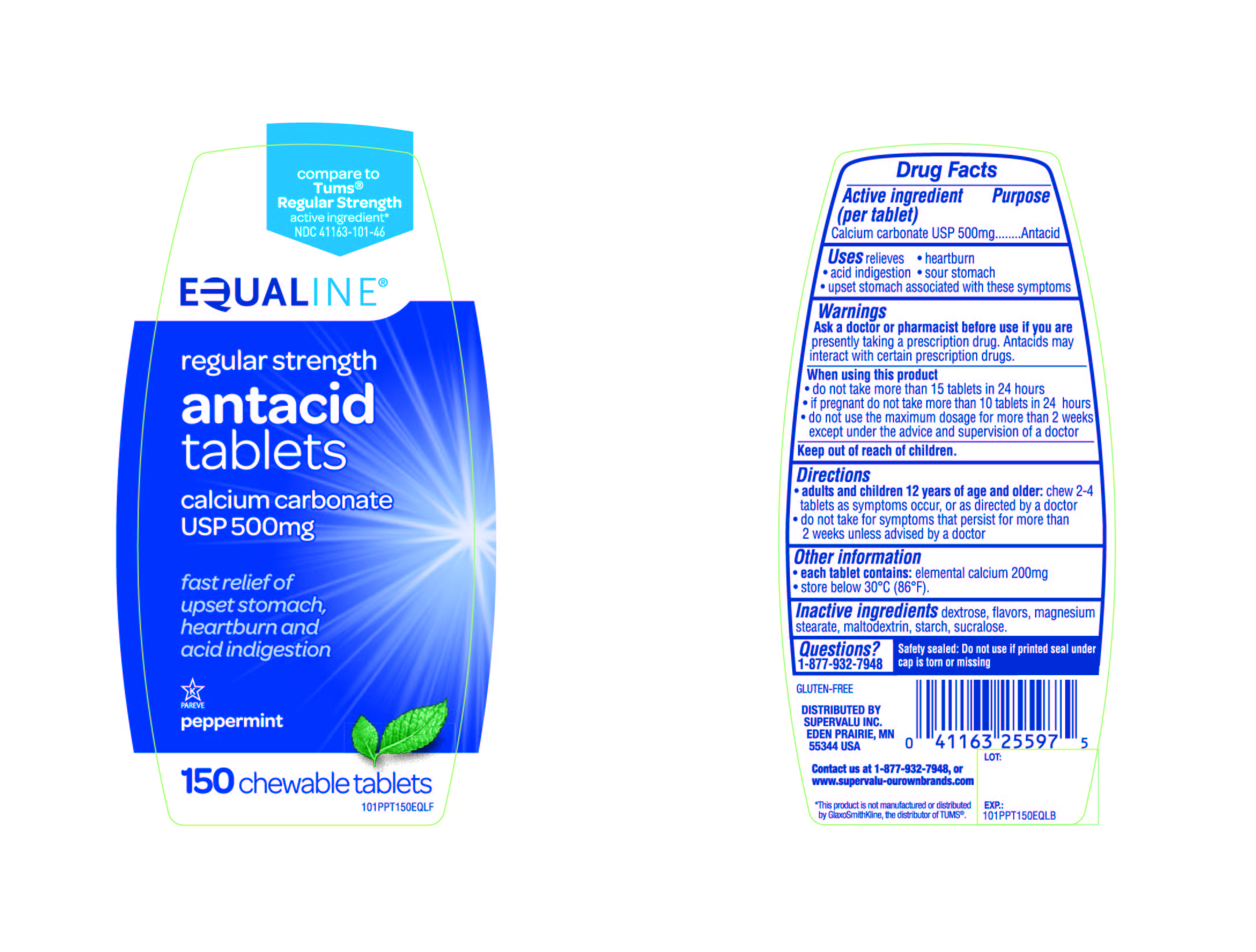 DRUG LABEL: EQUALINE regular strength antacid
NDC: 41163-101 | Form: TABLET, CHEWABLE
Manufacturer: SUPERVALU INC
Category: otc | Type: HUMAN OTC DRUG LABEL
Date: 20171227

ACTIVE INGREDIENTS: CALCIUM CARBONATE 500 mg/1 1
INACTIVE INGREDIENTS: DEXTROSE; MAGNESIUM STEARATE; MALTODEXTRIN; STARCH, CORN; SUCRALOSE

EQUALINE regular strength antacid calcium carbonate 500mg peppermint 150 chewable tablets

Active ingredient (per tablet)

Calcium carbonate USP 500mg

Purpose

Antacid

Uses

relieves

• heartburn

• acid indigestion

• sour stomach

• upset stomach associated with these symptoms

Warnings

Ask a doctor or pharmacist before use if you are presently taking a prescription drug. Antacids may interact with certain prescription drugs.

When using this product

- do not take more than 15 tablets in 24 hours
- if pregnant do not take more than 10 tablets in 24 hours
- do not use the maximum dosage for more than 2 weeks except under the advice and supervision of a doctor.

Directions

- adults and children 12 years of ageand older: chew 2-4 tablets as symptoms occur, or as directed by a doctor
- do not take for symptoms that persist for more than 2 weeks unless advised by a doctor

Other information

- each tablet contains: elemental calcium 200mg
- store below 30°C (86°F).

Inactive ingredients

dextrose, flavors, magnesium stearate, maltodextrin, starch, sucralose.

Questions?

1-877-932-7948

Safety sealed: Do not use if printed seal under cap is torn or missing

Package/Label Principal Display Panel

Compare to Tums® Regular Strength active ingredient*

NDC 41163-101-46

EQUALINE®

regular strength

antacid

tablets

calcium carbonate

USP 500 mg

fast relief of upset stomach,

heartburn and

acid indigestion

peppermint

150chewable tablets

GLUTEN- FREE

DISTRIBUTED BY

SUPERVALU INC.

EDEN PRAIRIE, MN

55344 USA

Contact us at 1-877-932-7948, or www.supervalu-ourownbrands.com

*This product is not manufactured or distributed by GlaxoSmithKline, the distributor of TUMS®.